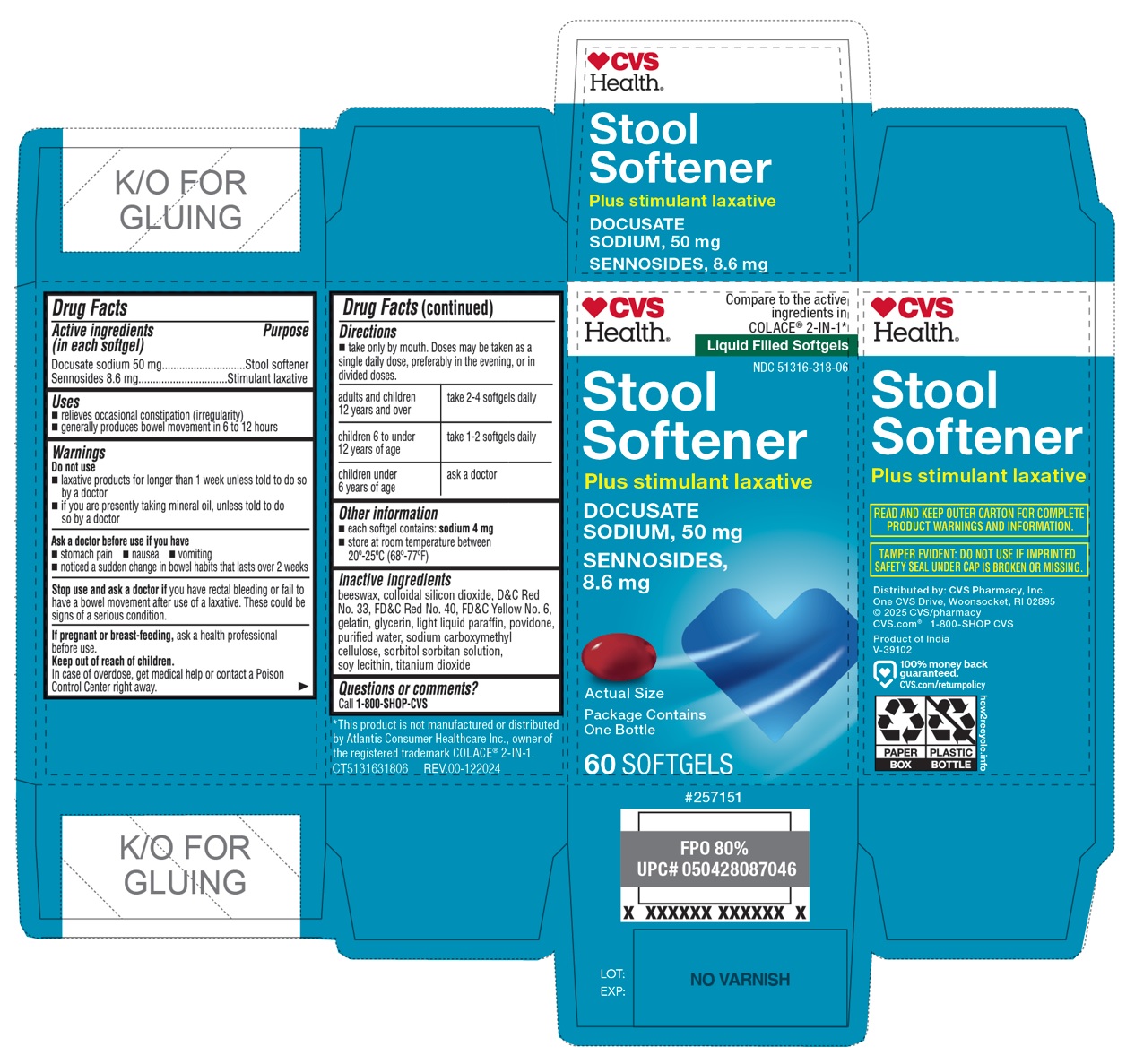 DRUG LABEL: CVS Health Stool Softener Plus stimulant laxative Softgel
NDC: 51316-318 | Form: CAPSULE, LIQUID FILLED
Manufacturer: CVS Pharmacy, Inc
Category: otc | Type: HUMAN OTC DRUG LABEL
Date: 20250319

ACTIVE INGREDIENTS: DOCUSATE SODIUM 50 mg/1 1; SENNOSIDES 8.6 mg/1 1
INACTIVE INGREDIENTS: YELLOW WAX; SILICON DIOXIDE; D&C RED NO. 33; FD&C RED NO. 40; FD&C YELLOW NO. 6; GELATIN, UNSPECIFIED; GLYCERIN; LIGHT MINERAL OIL; POVIDONE, UNSPECIFIED; WATER; CARBOXYMETHYLCELLULOSE SODIUM, UNSPECIFIED; SORBITOL; SORBITAN; SOYBEAN LECITHIN; TITANIUM DIOXIDE

CVS Health Stool Softener Plus stimulant laxative Softgel

Active ingredients (in each softgel)

Docusate sodium 50 mg

Sennosides 8.6 mg

Purpose

Stool softener

Stimulant laxative

Uses

• relieves occasional constipation (irregularity)
• generally produces bowel movement in 6 to 12 hours

Warnings

Do not use
• laxative products for longer than 1 week unless told to do so by a doctor
• if you are presently taking mineral oil, unless told to do so by a doctor

Ask a doctor before use if you have
• stomach pain • nausea • vomiting
• noticed a sudden change in bowel habits that lasts over 2 weeks

Stop use and ask a doctor if you have rectal bleeding or fail to have a bowel movement after use of a laxative. These could be signs of a serious condition.

If pregnant or breast-feeding, ask a health professional before use.

Keep out of reach of children. In case of overdose, get medical help or contact a Poison Control Center right away.

Directions

• take only by mouth. Doses may be taken as a single daily dose, preferably in the evening, or in divided doses.

adults and children 12 years and over | take 2-4 softgels daily
children 6 to under 12 years of age | take 1-2 softgels daily
children under 6 years of age | ask a doctor

Other information

• each softgel contains: sodium 4 mg

• store at room temperature between 20°-25°C (68°-77°F)

Inactive ingredients

beeswax, colloidal silicon dioxide, D&C Red No. 33, FD&C Red No. 40, FD&C Yellow No. 6, gelatin, glycerin, light liquid paraffin, povidone, purified water, sodium carboxymethyl cellulose, sorbitol sorbitan solution, soy lecithin, titanium dioxide

Questions or comments?

Call 1-800-SHOP-CVS

Compare to the active ingredients in COLACE® 2-IN-1*

Liquid Filled Softgels

Package Contains One Bottle

READ AND KEEP OUTER CARTON FOR COMPLETE PRODUCT WARNINGS AND INFORMATION.

TAMPER EVIDENT: DO NOT USE IF IMPRINTED SAFETY SEAL UNDER CAP IS BROKEN OR MISSING.

Distributed by: CVS Pharmacy, Inc.
One CVS Drive, Woonsocket, RI 02895
© 2025 CVS/pharmacy
CVS.com® 1-800-SHOP CVS

Product of India

*This product is not manufactured or distributed by Atlantis Consumer Healthcare Inc., owner of the registered trademark COLACE® 2-IN-1.